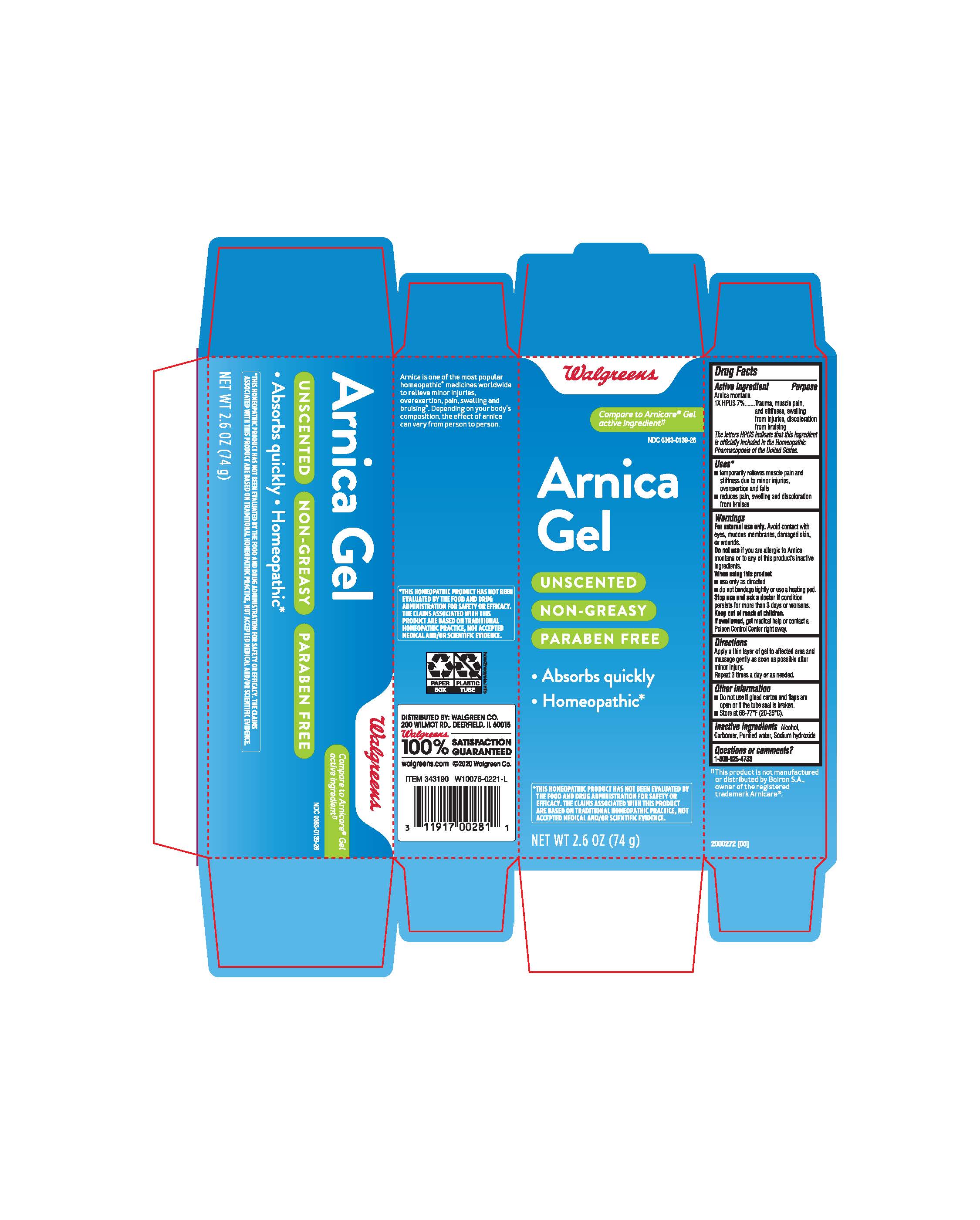 DRUG LABEL: Arnica gel
NDC: 0363-0139 | Form: GEL
Manufacturer: WALGREENS
Category: homeopathic | Type: HUMAN OTC DRUG LABEL
Date: 20210715

ACTIVE INGREDIENTS: ARNICA MONTANA 1 [hp_X]/1 g
INACTIVE INGREDIENTS: CARBOMER 940; SODIUM HYDROXIDE; ISOPROPYL ALCOHOL; WATER

Walgreens Arnica gel

Active ingredient

Arnica montana

1X HPUS 7%

Inactive ingredients

Alcohol, Carbomer, Purified water, Sodium Hydroxide

Dosage and administration

Apply a thin layer of gel to affected area and massage gently as soon as possible after minor injury. Repeat 3 times a day or as needed.

Uses*

- temporarily relieves muscel pain and stiffness due to minor injuries, over exertion and falls
- reduces pain, swelling and discoloration from bruises

Warnings

For external use only. Avoid contact with eyes, mucous membranes, damaged skin, or wounds.

Do not use if you are allergic to Arnica montana or to any of thus product's inactive ingredients.

When using this product

- use only as directed
- do not bandage tightly or use a heating pad.

Stop use and ask a doctor if condition persists for more than 3 days or worsens.

keep out of reach of children

If swallowed, get medical help or contact a Poison Control Center right away.

PURPOSE

Trauma, muscle pain, and, stiffness, swelling from injuries, discoloration from bruising

Other information

- Do not use if glued carton end flaps are open or if the tube seal is broken,
- Store at 68-77 F (20-25 C)

Questions or comments?

1-800-925-4733